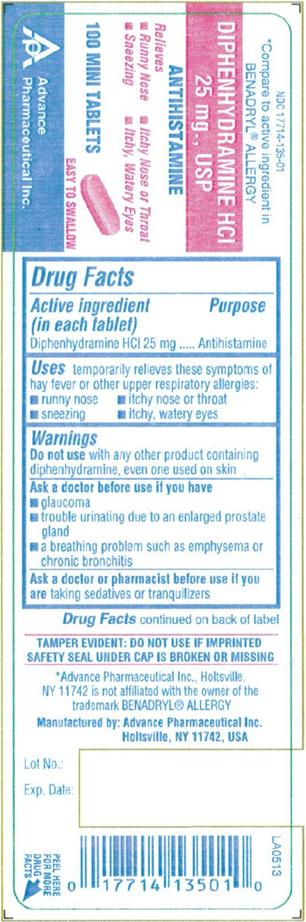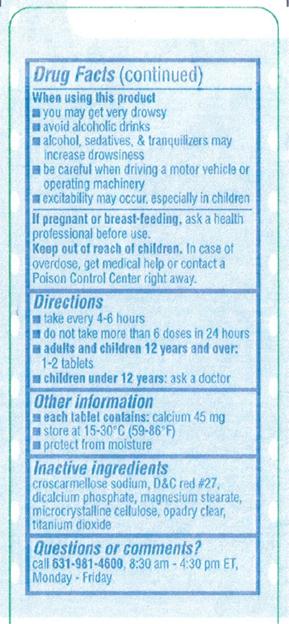 DRUG LABEL: Diphenhydramine Hydrochloride
NDC: 17714-135 | Form: TABLET
Manufacturer: Advance Pharmaceutical Inc.
Category: otc | Type: HUMAN OTC DRUG LABEL
Date: 20171222

ACTIVE INGREDIENTS: DIPHENHYDRAMINE HYDROCHLORIDE 25 mg/1 1
INACTIVE INGREDIENTS: CROSCARMELLOSE SODIUM; D&C RED NO. 27; DIBASIC CALCIUM PHOSPHATE DIHYDRATE; MAGNESIUM STEARATE; CELLULOSE, MICROCRYSTALLINE; TITANIUM DIOXIDE

DIPHENHYDRAMINE HCl 25mg, USP

Active Ingredient

(in each tablet)

Diphenhydramine HCl 25 mg

Purpose

Antihistamine

Uses

temporarily relieves these symptoms of hay fever or other upper respiratory allergies:

- runny nose
- itchy nose or throat
- sneezing
- itchy, watery eyes

Warnings

Do not use with any other product containing diphenhydramine, even one used on skin

Ask a doctor before use if you have

- glaucoma
- trouble urinating due to an enlarged prostate gland
- a breathing problem such as emphysema or chronic bronchitis
  Ask a doctor or pharmacist before use if you are taking sedatives or tranquilizers
  When using this product
- you may get very drowsy
- avoid alcoholic drinks
- alcohol, sedatives & tranquilizers may increase drowsiness
- be careful when driving a motor vehicle or operating machinery
- excitability may occur, especially in children
  If pregnant or breast-feeding, ask a health professional before use.

Keep out of reach of children.

In case of overdose, get medical help or contact a Poison Control Center right away.

Directions

- take every 4-6 hours
- do not take more than 6 doses in 24 hours
- adults and children 12 years and over : 1-2 tablets
- children under 12 years: ask a doctor

Other Information

- each tablet contains: calcium 45 mg
- store at 15-30 °C (59-86 °F)
- protect from moisture

Inactive Ingredients

croscarmellose sodium, D&C red# 27, dicalcium phosphate, magnesium stearate, microcrystalline cellulose, opadry clear, titanium dioxide

Questions or Comments

TAMPER EVIDENT: DO NOT USE IF IMPRINTED SAFETY SEAL UNDER CAP IS BOKEN OR MISSING

Manufactured by: Advance Pharmaceutical, Inc. Holtsville, NY 11742

PACKAGE LABEL.PRINCIPAL DISPLAY PANEL

DIPHENHYDRAMINE HYDROCHLORIDE TABLETx`, USP 25 MG

ANTIHISTAMINE

NDC: 17714-135-01 – 100 MINI TABLETS